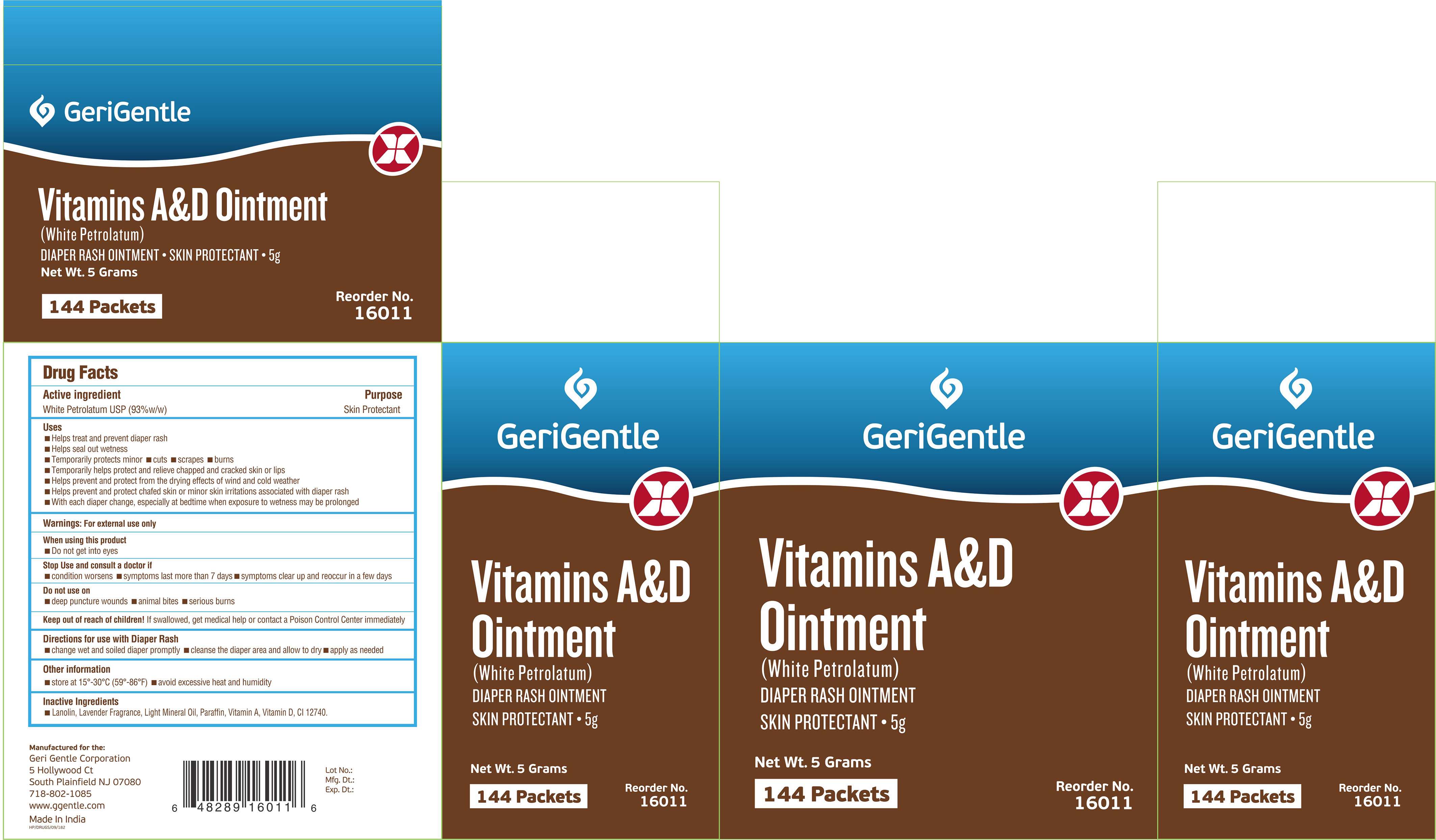 DRUG LABEL: Gerigentle-Vitamins A and D
NDC: 69771-105 | Form: OINTMENT
Manufacturer: Geri-Gentle Corporation
Category: otc | Type: HUMAN OTC DRUG LABEL
Date: 20251017

ACTIVE INGREDIENTS: PETROLATUM 0.93 g/1 g
INACTIVE INGREDIENTS: LANOLIN; PARAFFIN; LIGHT MINERAL OIL; SOLVENT YELLOW 18; VITAMIN A; VITAMIN D

Gerigentle-Vitamins A and D

Drug Facts

Active ingredient

White Petrolatum USP (93%w/w)

Purpose

Skin Protectant

Uses

- Helps treat and prevent diaper rash
- Helps seal out wetness
- Temporarily protects minor
  - cuts
  - scrapes
  - burns
- Temporarily helps protect and relieve chapped and cracked skin or lips
- Helps prevent and protect from the drying effects of wind and cold weather
- Helps prevent and protect chafed skin or minor skin irritations associated with diaper rash
- With each diaper change, especially at bedtime when exposure to wetness may be prolonged

Warnings

For external use only

When using this product

- Do not get into eyes

Stop Use and consult a doctor if

- condition worsens
- symptoms last more than 7 days
- symptoms clear up and reoccur in a few days

Do not use on

- deep puncture wounds
- animal bites
- serious burns

Keep out of reach of children!If swallowed, get medical help or contact a Poison Control Center immediately

Directions for use with Diaper Rash

- change wet and soiled diaper promptly
- cleanse the diaper area and allow to dry
- apply as needed

Other information

- store at 15°-30°C (59°-86°F)
- avoid excessive heat and humidity

Inactive Ingredients

- Lanolin, Lavender Fragrance, Light Liquid Paraffin, Paraffin, Vitamin A, Vitamin D, CI 12740